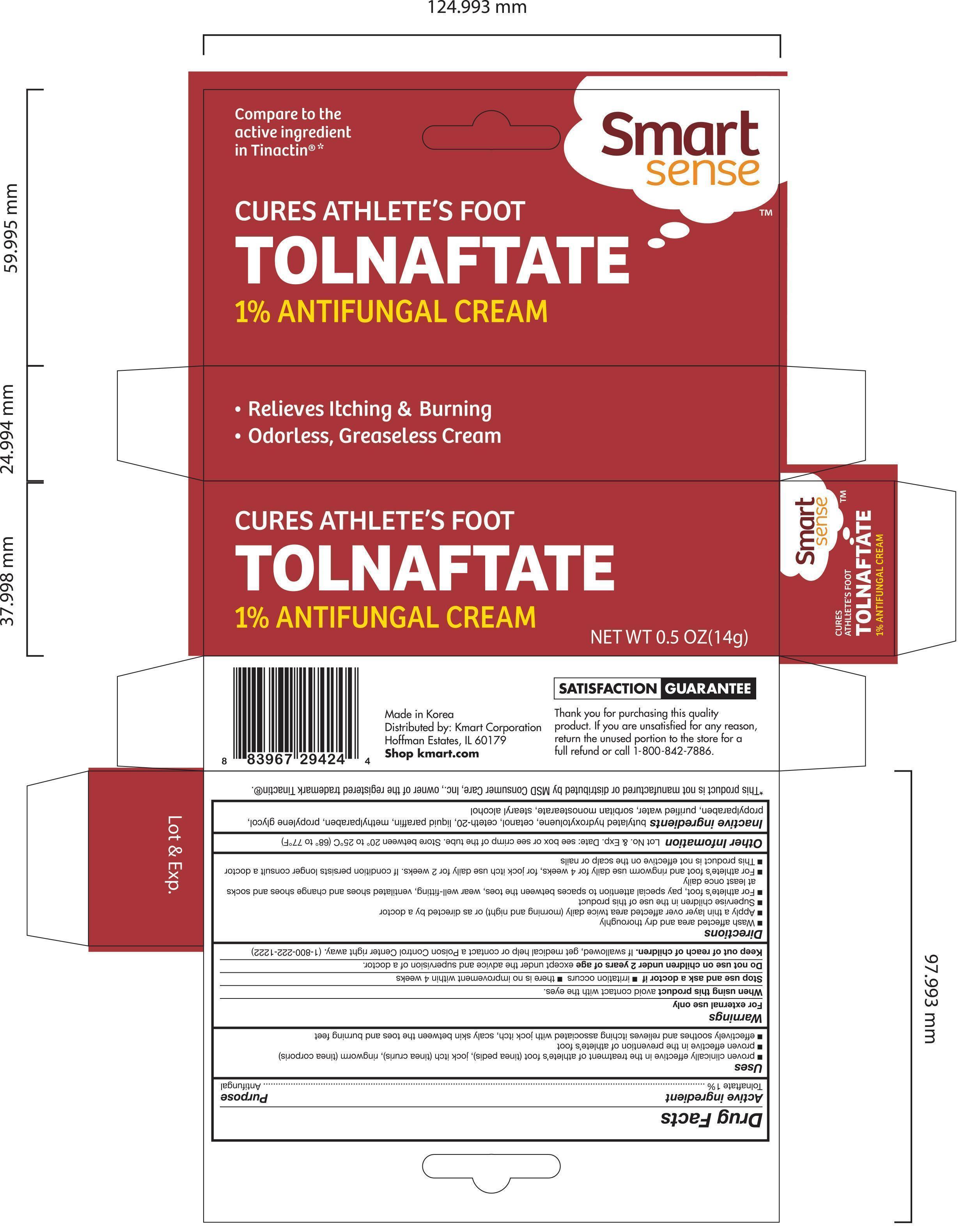 DRUG LABEL: Smart Sense Tolnaftate Antifungal
NDC: 49738-424 | Form: CREAM
Manufacturer: Kmart Corporation
Category: otc | Type: HUMAN OTC DRUG LABEL
Date: 20140923

ACTIVE INGREDIENTS: TOLNAFTATE 10 mg/1 g
INACTIVE INGREDIENTS: BUTYLATED HYDROXYTOLUENE; CETETH-20; PARAFFIN; METHYLPARABEN; PROPYLENE GLYCOL; PROPYLPARABEN; WATER; SORBITAN MONOSTEARATE; ALCOHOL

Active ingredient Purpose

Tolnaftate 1%............................................... Antifungal

Uses

- proved clinically effective in the treatment of athlete's foot (tinea pedis), jock itch (tinea cruris), ringworm (tinea corporis)
- proven effective in the prevention of athlete's foot
- effectively soothes and relieves itching associated with jock itch, scaly skin between

Warnings

For external use only

Stop use and ask a doctor if

- irritation occurs
- there is no improvement within 4 weeks

Do not use on children under 2 years og age except under the advice and supervision of a doctor

Keep out of reach of children. If swallowed, get medical help or contact a Poision Control Center right away. (1-800-222-1222)

Directions

- Wash affected area and dry thoroughly
- Apply a thin layer over affected area twice daily (morning and night) or as directed by a doctor
- Supervise children in the use of this product
- For athlete's foot, pay special attention to spaces between the toes, wear well-fitting, ventilated shoes and chage shoes and socks at least once daily
- For athlete's foot and ringworm use daily for 4 weeks, for jock itch use daily for 2 weeks. If condition persists longer consult a doctor
- This product is not effective on the scalp or nails

Other information

Lot No. & Exp. Date: see box or see crimp of the tube. Store between 20° to 25°C (68° to 77°F)

INACTIVE INGREDIENT

Inactive ingredients butylated hydroxytoluene, cetanol, ceteth-20, liquid paraffin, methylparaben, propylene glycol, propylparaben, purified water, sorbitan monostearate, stearyl alcohol

DOSAGE AND ADMINISTRATION

DISTRIBUTED BY:

Kmart Corporation

Hoffman Estates, IL 60179

Made in Korea